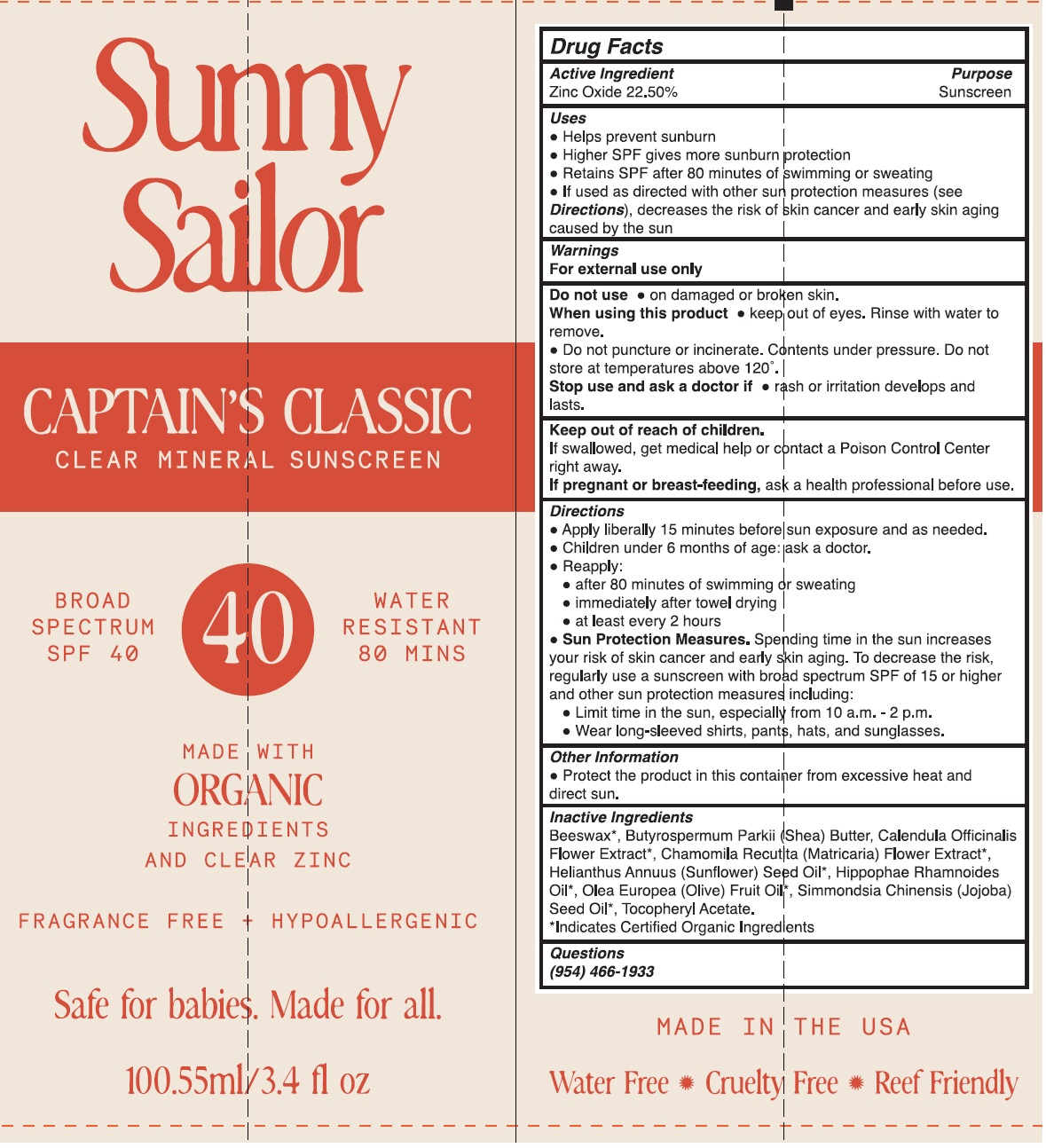 DRUG LABEL: Sunny Sailor Captain s Classic Clear Mineral Sunscreen SPF 40
NDC: 85135-577 | Form: CREAM
Manufacturer: SUNNY SAILOR LLC
Category: otc | Type: HUMAN OTC DRUG LABEL
Date: 20250115

ACTIVE INGREDIENTS: ZINC OXIDE 225 mg/1 mL
INACTIVE INGREDIENTS: YELLOW WAX; SHEA BUTTER; CALENDULA OFFICINALIS FLOWER; CHAMOMILE; SUNFLOWER OIL; OLIVE OIL; JOJOBA OIL; .ALPHA.-TOCOPHEROL ACETATE

Sunny Sailor Captain's Classic Clear Mineral Sunscreen SPF 40

Active Ingredient

Zinc Oxide 22.50%

Purpose

Sunscreen

Uses

- Helps prevent sunburn
- Higher SPF gives more sunburn protection
- Retains SPF after 80 minutes of swimming or sweating
- If used as directed with other sun protection measures (see Directions), decreases the risk of skin cancer and early skin aging caused by the sun

Warnings

For external use only

Do not use

- on damaged or broken skin.

When using this product

- keep out of eyes. Rinse with water to remove.
- Do not puncture or incinerate. Contents under pressure. Do not store at temperatures above 120°.

Stop use and ask a doctor if

- rash or irritation develops and lasts.

Keep out of reach of children.

- If swallowed, get medical help or contact a Poison Control Center right away.

If pregnant or breast-feeding,

ask health professional before use.

Directions

- Apply liberally 15 minutes before sun exposure and as needed.
- Children under 6 months of age: ask a doctor.
- Reapply:
- after 80 minutes of swimming or sweating
- immediately after towel drying
- at least every 2 hours
- Sun Protection Measures.Spending time in the sun increases your risk of skin cancer and early skin aging. To decrease the risk, regularly use a sunscreen with broad spectrum SPF of 15 or higher and other sun protection measures including:
- Limit time in the sun, especially from 10a.m.- 2 p.m.
- Wear long-sleeved shirts, pants, hats, and sunglasses.

Other Information

- Protect the product in this container from excessive heat and direct sun.

Inactive Ingredients

Beeswax*, Butyrospermum Parkii (Shea) Butter, Calendula Officinalis Flower Extract*, Chamomila Recutita (Matricaria) Flower Extract*, Helianthus Annuus (Sunflower) Seed Oil*, Hippophae Rhamnoides Oil*, Olea Europea (Olive) Fruit Oil*, Simmondsia Chinensis (Jojoba) Seed Oil*, Tocopheryl Acetate.

* Indicates Certified Organic Ingredients

Questions

(954) 466-1933